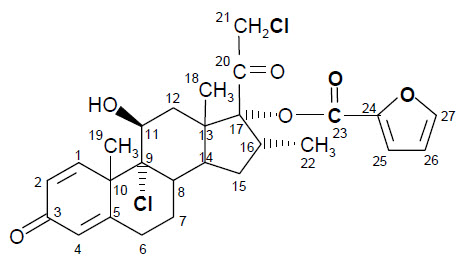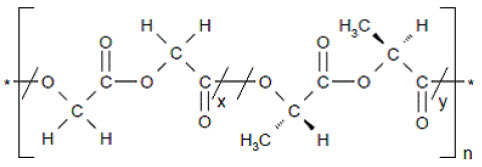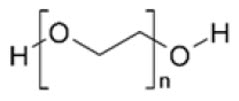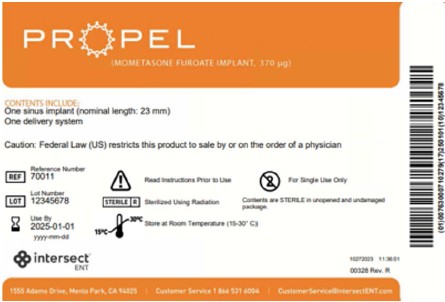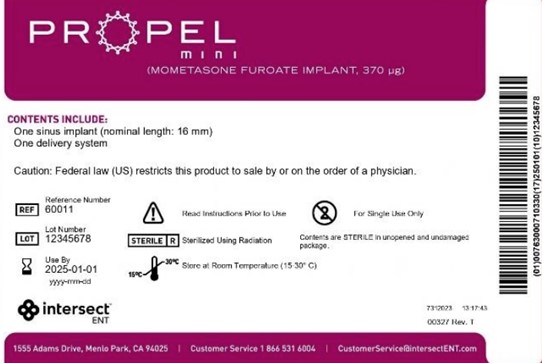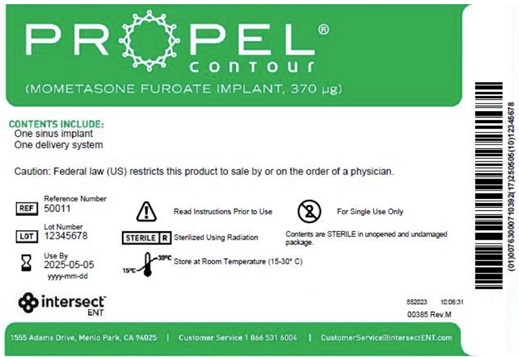 DRUG LABEL: Propel
NDC: 10599-000 | Form: KIT | Route: NASAL
Manufacturer: Intersect ENT, INC.
Category: other | Type: MEDICAL DEVICE
Date: 20241231

ACTIVE INGREDIENTS: MOMETASONE FUROATE 370 ug/1 1
INACTIVE INGREDIENTS: POLYETHYLENE GLYCOL, UNSPECIFIED; POLY(DL-LACTIC-CO-GLYCOLIC ACID), (50:50; 12000 MW); POLYETHYLENE GLYCOL, UNSPECIFIED

Propel®/Propel® mini/Propel® Contour
(mometasone furoate implant, 370 µg)

DEVICE DESCRIPTION

The Propel/Propel mini/Propel Contour sinus implant is a bioabsorbable implant designed to maintain patency of the sinus cavity (Propel/Propel mini) or sinus ostium (Propel Contour). The Propel/Propel mini/Propel Contour implant is manufactured from a synthetic bioabsorbable copolymer, poly (L-lactide-co-glycolide) (PLG). The implant contains mometasone furoate (active ingredient), a synthetic corticosteroid with anti-inflammatory activity. Mometasone furoate is a white to off-white powder. The chemical name is 9α,21-dichloro-11β,17α-dihydroxy-16α-methylpregna-1,4-diene-3,20-dione 17-(2-furoate), with the empirical formula C27H30Cl2O6, and a molecular weight of 521.43 g/mol. Mometasone furoate is a hydrophobic drug that is practically insoluble in water. Mometasone furoate is stable under aqueous, acidic and oxidative conditions. Mometasone furoate can degrade under extreme basic, thermal and photolytic conditions. The chemical structure is shown. The drug is embedded in a bioabsorbable polymer matrix containing poly-(DL-lactide-co-glycolide) and polyethylene glycol (inactive ingredients) which provides for gradual release of the drug.

Chemical structure of mometasone furoate

Chemical structure of mometasone furoate

The inactive ingredients on the sinus implant are poly-(DL-lactide-co-glycolide) and polyethylene glycol. Poly-(DL-lactide-co-glycolide) is an amorphous biodegradable polymer. The chemical structure is shown below.

Chemical structure of poly-(DL-lactide-co-glycolide)

Chemical structure of poly-(DL-lactide-co-glycolide)

Polyethylene glycol is a hydrophilic polyether compound that is highly flexible. It is non-toxic and non-immunogenic. The chemical structure is shown below.

Chemical structure of polyethylene glycol

Chemical structure of polyethylene glycol

The implant is designed to accommodate the size and variability of the post-surgical ethmoid sinus anatomy (for Propel), ethmoid or frontal sinus anatomy (for Propel mini), and frontal or maxillary sinus ostium anatomy for Propel Contour. The Propel/Propel mini/Propel Contour implant is designed to be inserted by a physician under endoscopic visualization and once inserted, the implant is designed to be self-retaining against the mucosa of the surgically enlarged sinus (Propel/Propel mini) or sinus ostium (Propel Contour). A delivery system is provided to access the ethmoid sinus (for Propel), ethmoid or frontal sinus (for Propel mini), and frontal or maxillary sinus ostium (for the Propel Contour) and insert the implant.

INDICATIONS FOR USE

The Propel sinus implant is intended for use in patients ≥ 18 years of age following ethmoid sinus surgery to maintain patency, thereby reducing the need for post-operative intervention such as surgical adhesion lysis and/or use of oral steroids. The Propel implant separates mucosal tissues, provides stabilization of the middle turbinate, prevents obstruction by adhesions, and reduces edema.

The Propel mini sinus implant is intended for use in patients ≥ 18 years of age following ethmoid/frontal sinus surgery to maintain patency of the ethmoid sinus or frontal sinus opening. The Propel mini sinus implant separates/dilates surrounding mucosal tissues, provides stabilization of the middle turbinate, prevents obstruction by adhesions, and reduces inflammation. The implant reduces the need for post-operative intervention such as surgical adhesion lysis and/or use of oral steroids.

The Propel Contour sinus implant is intended for use in patients ≥ 18 years of age to maintain patency of the frontal and maxillary sinus ostia following sinus surgery and locally deliver steroids to the sinus mucosa. The PROPEL Contour sinus implant separates/dilates mucosal tissues, prevents obstruction by adhesions/scarring, and reduces edema. The implant reduces the need for post-operative intervention such as surgical adhesion lysis and/or use of oral steroids.

CONTRAINDICATIONS

The use of the Propel/Propel mini/Propel Contour sinus implant is contraindicated in the following patients:

•Patients with suspected or confirmed hypersensitivity and / or intolerance to mometasone furoate.
•Patients with a known hypersensitivity to lactide, glycolide or caprolactone copolymers.

WARNINGS AND PRECAUTIONS

WARNINGS

- The Propel/Propel mini/Propel Contour sinus implant is designed for single patient use only. Do not reprocess or reuse.
- Do not use if the package is open or damaged.

PRECAUTIONS

- Special care should be taken to avoid bending, twisting or damaging the implant.
- The implant is not designed to be modified by the physician.
- The implant is not intended to be compressed and loaded into the delivery system more than two times.
- The implant must be placed under endoscopic visualization.
- The implant exhibits no antimicrobial properties.
- Foreign body reaction may occur as is possible with most surgical adjuncts.
- In rare instances, the physiochemical condition associated with sinus surgery, both with and without sinus implants or packing, may present a risk of toxic shock syndrome (TSS).
- Pediatric Use: The safety and effectiveness of the implant in pediatric patients have not been established.
- Pregnancy and Nursing Females: The safety and effectiveness of the implant in pregnant or nursing females have not been established.

DRUG INFORMATION

MECHANISM OF ACTION: Corticosteroids have been shown to have a wide range of effects on multiple cell types (e.g., mast cells, eosinophils, neutrophils, macrophages, and lymphocytes) and mediators (e.g., histamine, eicosanoids, leukotrienes, and cytokines) involved in inflammation. The precise mechanism behind the anti-inflammatory properties of the eluted mometasone furoate is not known.

PHARMACOKINETICS: The Propel sinus implant underwent pharmacokinetics testing. Following bilateral drug-eluting Propel implant placement after sinus surgery for chronic sinusitis and subsequent weekly morning blood sampling for 4 weeks in 5 adult patients, plasma mometasone furoate concentrations were not quantifiable at any time point. Mean cortisol concentrations were within normal limits.

DRUG INTERACTIONS

No drug-drug interaction studies have been conducted with the Propel/Propel mini/Propel Contour implant.

CARCINOGENICITY, GENOTOXICITY AND REPRODUCTIVE TOXICITY

No long term studies in animals have been performed to evaluate the carcinogenic potential of the Propel/Propel mini/Propel Contour implant.

PREGNANCY

There have been no controlled studies in pregnant women using the Propel/Propel mini/Propel Contour implant. The Propel®/Propel® mini/Propel® Contour sinus implant should be used during pregnancy only if the potential benefits justify the potential risk.

LACTATION

It is not known if mometasone furoate is excreted in human milk. Because other corticosteroids are excreted in human milk, the Propel/Propel mini/Propel Contour sinus implant should be used only if the potential benefits justify the potential risk.

DOSAGE AND ADMINISTRATION

Each Propel/Propel mini/Propel Contour sinus implant contains 370µg of mometasone furoate which is gradually released over time.

I. POTENTIAL ADVERSE EFFECTS OF THE DEVICE ON HEALTH

Potential Adverse Effects: Potential adverse effects associated with the Propel/Propel mini/Propel Contour sinus implant are anticipated to be similar to those associated with other sinus stents, gels or packing.

Potential adverse effects associated with the Propel/Propel mini/Propel Contour sinus implant include, but may not be limited to:

- Premature displacement of implant or implant fragments
- Swallowing implant or implant fragments
- Pain/pressure/headache may result from the adherence of crusting to, or presence of the implant
- Aspiration of small implant fragments (not observed in clinical trials)
- Foreign body response, including formation of granulation tissue

Potential risks or side effects associated with intranasal mometasone furoate include:

- nasal irritation
- hypersensitivity reaction
- intranasal bleeding
- localized infection (bacterial, fungal or viral) in the nose or pharynx
- nasal burning
- nasal dryness
- susceptibility to secondary infections due to bacteria, fungi or viruses
- glaucoma/elevation of intraocular pressure
- cataracts/change in lens opacities
- headache
- pharyngitis

Potential risks or general side effects associated with steroids:

- alteration of the HPA axis including growth suppression
- immunosuppression
- hypersensitivity reactions
- headache
- epistaxis
- coughing
- vomiting
- candidiasis
- glaucoma/elevation in intraocular pressure
- cataracts/changes in lens opacities
- arthralgia
- myalgia

Manufactured by:

Intersect ENT Inc.
1555 Adams Drive
Menlo Park, CA 94025
650-641-2100
www.intersectENT.com

Customer Service 1-866-531-6004
CustomerService@intersectENT.com

PACKAGE/LABEL PRINCIPAL DISPLAY PANEL – Propel®

Picture of label is representative of label content

Propel®
(MOMETASONE FUROATE IMPLANT, 370 µg)
CONTENTS INCLUDE:

One sinus implant (nominal length: 23 mm)
One delivery system
Caution: Federal law (US) restricts this product to sale by or on the order of a physician.

Reference Number 70011 | Read Instructions Prior to Use | For Single Use Only
Lot Number 12345678 | Sterilized Using Radiation | Contents are STERILE in unopened and undamaged package
Use By 2025-01-01 yyyy-mm-dd | Store at Room Temperature (15-30° C)

intersect® ENT

12272023 11:30:01
00328 Rev. R

1555 Adams Drive, Menlo Park, CA 94025 | Customer Service 1-866-531-6004 | CustomerService@intersectENT.com

PACKAGE/LABEL PRINCIPAL DISPLAY PANEL – Propel® mini

Picture of label is representative of label content

Propel® mini
(MOMETASONE FUROATE IMPLANT, 370 µg)
CONTENTS INCLUDE:

One sinus implant (nominal length: 16 mm)
One delivery system
Caution: Federal law (US) restricts this product to sale by or on the order of a physician.

Reference Number 60011 | Read Instructions Prior to Use | For Single Use Only
Lot Number 12345678 | Sterilized Using Radiation | Contents are STERILE in unopened and undamaged package.
Use By 2025-01-01 yyyy-mm-dd | Store at Room Temperature (15-30° C)

intersect® ENT

7312023 13:17:43
00327 Rev. T
1555 Adams Drive, Menlo Park, CA 94025 | Customer Service 1-866-531-6004 | CustomerService@intersectENT.com

PACKAGE/LABEL PRINCIPAL DISPLAY PANEL – Propel® Contour

Picture of label is representative of label content

Propel® Contour
(MOMETASONE FUROATE IMPLANT, 370 µg)
CONTENTS INCLUDE:

One sinus implant
One delivery system
Caution: Federal law (US) restricts this product to sale by or on the order of a physician.

Reference Number 50011 | Read Instructions Prior to Use | For Single Use Only
Lot Number 12345678 | Sterilized Using Radiation | Contents are STERILE in unopened and undamaged package.
Use By 2025-05-05 yyyy-mm-dd | Store at Room Temperature (15-30° C)

intersect® ENT

552023 10:06:31
00385 Rev. M
1555 Adams Drive, Menlo Park, CA 94025 | Customer Service 1-866-531-6004 | CustomerService@intersectENT.com